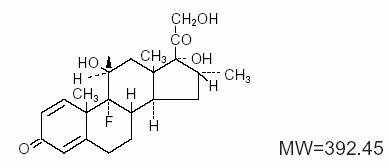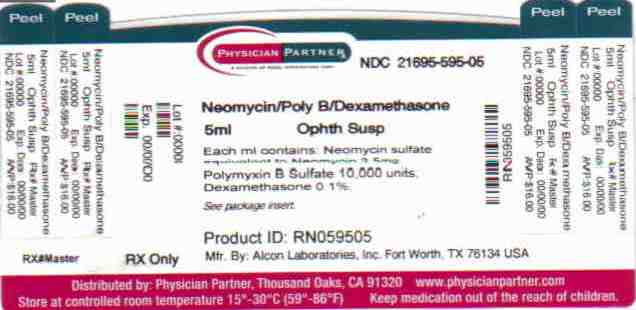 DRUG LABEL: Neomycin and Polymyxin B Sulfates and Dexamethasone
NDC: 21695-595 | Form: SUSPENSION
Manufacturer: Rebel Distributors Corp
Category: prescription | Type: HUMAN PRESCRIPTION DRUG LABEL
Date: 20101008

ACTIVE INGREDIENTS: neomycin sulfate 3.5 mg/1 mL; polymyxin B sulfate 10000 mg/1 mL; dexamethasone 1 mg/1 mL
INACTIVE INGREDIENTS: BENZALKONIUM CHLORIDE; HYPROMELLOSE 2910 (15 MPA.S); sodium chloride; POLYSORBATE 20; HYDROCHLORIC ACID; water

Neomycin and Polymyxin B Sulfates
and Dexamethasone Ophthalmic
Suspension
Sterile

DESCRIPTION

Neomycin and polymyxin B sulfates and dexamethasone ophthalmic suspension is a multiple dose anti-infective steroid combination in sterile suspension form for topical application. The chemical structure for the active ingredient, dexamethasone, is:

Established Name:

dexamethasone

Chemical Name:

pregna-1, 4-diene-3, 20-dione, 9-fluoro-11,17, 21-trihydroxy-16-methyl-, (11β, 16α)-.

The other active ingredients are neomycin sulfate and polymyxin B sulfate.

Each mL contains: Actives: neomycin sulfate equivalent to neomycin 3.5 mg, polymyxin B sulfate 10,000 units, dexamethasone 0.1%. Preservative: benzalkonium chloride 0.004%. Vehicle: hypromellose 2910 0.5%. Inactives: sodium chloride, polysorbate 20, hydrochloric acid and/or sodium hydroxide (to adjust pH), purified water.

CLINICAL PHARMACOLOGY

Corticosteroids suppress the inflammatory response to a variety of agents and they probably delay or slow healing. Since corticosteroids may inhibit the body’s defense mechanism against infection, a concomitant antimicrobial drug may be used when this inhibition is considered to be clinically significant in a particular case.

When a decision to administer both a corticosteroid and an antimicrobial is made, the administration of such drugs in combination has the advantage of greater patient compliance and convenience, with the added assurance that the appropriate dosage of both drugs is administered, plus assured compatibility of ingredients when both types of drugs are in the same formulation and, particularly, that the correct volume of drug is delivered and retained.

The relative potency of corticosteroids depends on the molecular structure, concentration and release from the vehicle.

INDICATIONS AND USAGE

For steroid-responsive inflammatory ocular conditions for which a corticosteroid is indicated and where bacterial infection or a risk of bacterial ocular infection exists.

Ocular corticosteroids are indicated in inflammatory conditions of the palpebral and bulbar conjunctiva, cornea, and anterior segment of the globe where the inherent risk of corticosteroids use in certain infective conjunctivitides is accepted to obtain a diminution in edema and inflammation. They are also indicated in chronic anterior uveitis and corneal injury from chemical, radiation or thermal burns; or penetration of foreign bodies.

The use of a combination drug with an anti-infective component is indicated where the risk of infection is high or where there is an expectation that potentially dangerous numbers of bacteria will be present in the eye.

The particular anti-infective drug in this product is active against the following common bacterial eye pathogens: Staphylococcus aureus, Escherichia coli, Haemophilus influenzae, Klebsiella/Enterobacter species, Neisseria species, and Pseudomonas aeruginosa.

This product does not provide adequate coverage against: Serratia marcescens and streptococci, including Streptococcus pneumoniae.

CONTRAINDICATIONS

Epithelial herpes simplex keratitis (dendritic keratitis), vaccinia, varicella, and many other viral diseases of the cornea and conjunctiva. Mycobacterial infection of the eye. Fungal diseases of ocular structures. Hypersensitivity to a component of the medication. (Hypersensitivity to the antibiotic component occurs at a higher rate than for other components.)

WARNINGS

NOT FOR INJECTION. Do not touch dropper tip to any surface, as this may contaminate the contents. Prolonged use may result in glaucoma, with damage to the optic nerve, defects in visual acuity and fields of vision, and posterior subcapsular cataract formation. Prolonged use may suppress the host response and thus increase the hazard of secondary ocular infections. In those diseases causing thinning of the cornea or sclera, perforations have been known to occur with the use of topical corticosteroids. In acute purulent conditions of the eye, corticosteroids may mask infection or enhance existing infection. If this product is used for 10 days or longer, intraocular pressure should be routinely monitored even though it may be difficult in children and uncooperative patients.

Products containing neomycin sulfate may cause cutaneous sensitization.

Employment of corticosteroid medication in the treatment of herpes simplex requires great caution.

PRECAUTIONS

The initial prescription and renewal of the medication order beyond 20 mL should be made by a physician only after examination of the patient with the aid of magnification, such as a slit lamp biomicroscopy and, where appropriate, fluorescein staining.

The possibility of persistent fungal infections of the cornea should be considered after prolonged corticosteroid dosing.

Pregnancy

Pregnancy Category C. Dexamethasone has been shown to be teratogenic in mice and rabbits following topical ophthalmic application in multiples of the therapeutic dose.

In the mouse, corticosteroids produce fetal resorptions and a specific abnormality, cleft palate. In the rabbit, corticosteroids have produced fetal resorptions and multiple abnormalities involving the head, ears, limbs, palate, etc.

There are no adequate or well-controlled studies in pregnant women. Neomycin and polymyxin B sulfates and dexamethasone ophthalmic suspension should be used during pregnancy only if the potential benefit to the mother justifies the potential risk to the embryo or fetus. Infants born of mothers who have received substantial doses of corticosteroids during pregnancy should be observed carefully for signs of hypoadrenalism.

Nursing Mothers

Systemically administered corticosteroids appear in human milk and could suppress growth, interfere with endogenous corticosteroid production, or cause other untoward effects. It is not known whether topical administration of corticosteroids could result in sufficient systemic absorption to produce detectable quantities in human milk. Because many drugs are excreted in human milk, caution should be exercised when neomycin and polymyxin B sulfates and dexamethasone ophthalmic suspension is administered to a nursing woman.

Pediatric Use

Safety and effectiveness in pediatric patients have not been established.

ADVERSE REACTIONS

Adverse reactions have occurred with corticosteroid/anti-infective combination drugs which can be attributed to the corticosteroid component, the anti-infective component, or the combination.
Exact incidence figures are not available since no denominator of treated patients is available.
Reactions occurring most often from the presence of the anti-infective ingredient are allergic sensitizations.
The reactions due to the corticosteroid component are: elevation of intraocular pressure (IOP) with possible development of glaucoma, and infrequent optic nerve damage; posterior subcapsular cataract formation; and delayed wound healing.

Secondary Infection: The development of secondary infection has occurred after use of combinations containing corticosteroids and antimicrobials. Fungal infections of the cornea are particularly prone to develop coincidentally with long-term applications of corticosteroids. The possibility of fungal invasion must be considered in any persistent corneal ulceration where corticosteroid treatment has been used.

Secondary bacterial ocular infection following suppression of host responses also occurs.

DOSAGE AND ADMINISTRATION

One to two drops topically in the conjunctival sac(s). In severe disease, drops may be used hourly, being tapered to discontinuation as the inflammation subsides. In mild disease, drops may be used up to four to six times daily.

Not more than 20 mL should be prescribed initially and the prescription should not be refilled without further evaluation as outlined in PRECAUTIONS above.

FOR TOPICAL OPHTHALMIC USE ONLY.

HOW SUPPLIED

Sterile ophthalmic suspension in 5 mL plastic DROP-TAINER* dispenser (NDC 21695-595-05).

STORAGE: Store at 8°-27°C (46°-80°F).

Rx Only

*DROP-TAINER is a registered trademark of Alcon Manufacturing, Ltd.

Dist. by:
FALCON Pharmaceuticals, Ltd.
Fort Worth, Texas 76134 USA

Mfd by:
ALCON LABORATORIES, INC.
Fort Worth, Texas 76134 USA

Printed in USA

340905-0803

Repackaged by:

REBEL DISTRIBUTORS CORP

Thousand Oaks, CA 91320